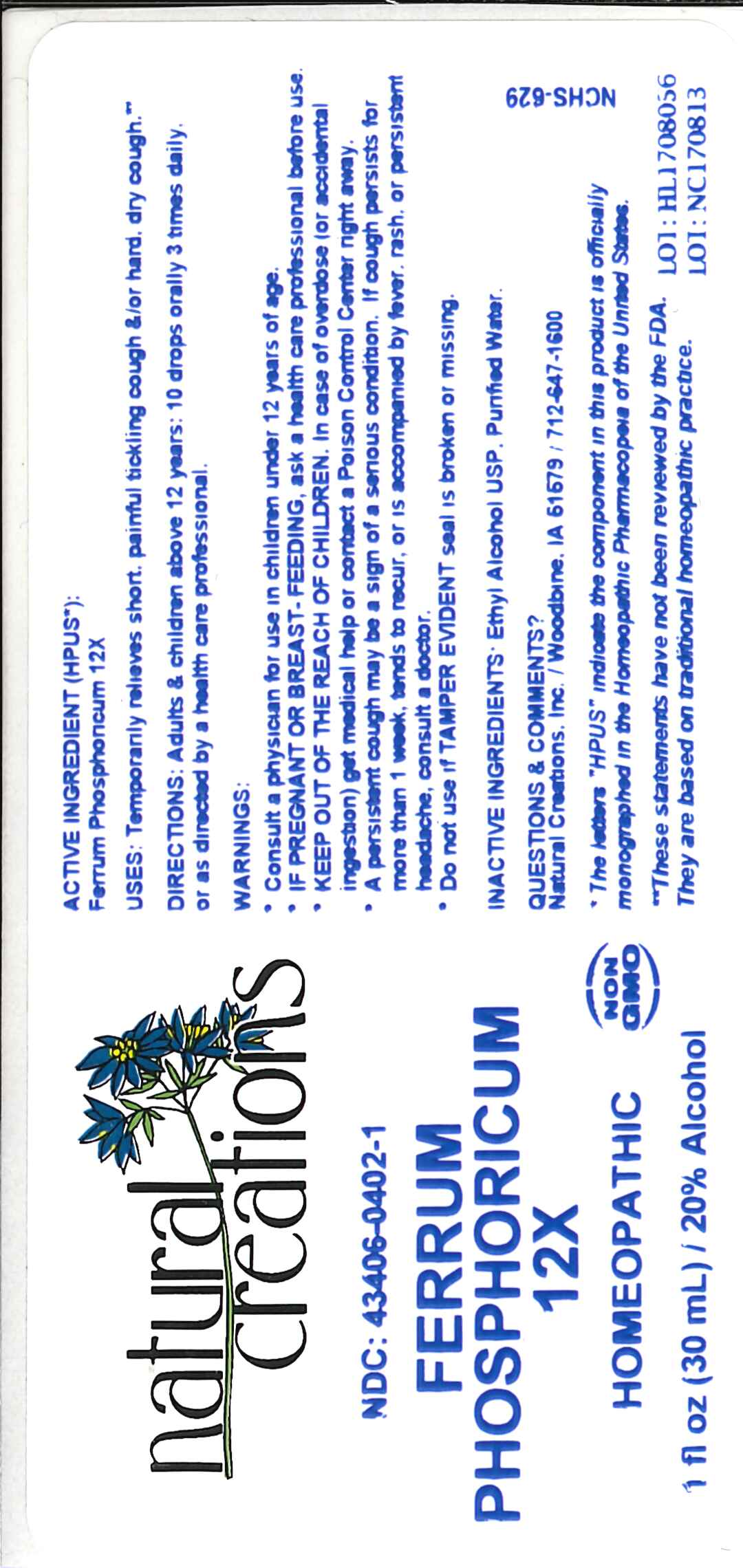 DRUG LABEL: FERRUM PHOSPHORICUM 12X
NDC: 43406-0402 | Form: LIQUID
Manufacturer: Natural Creations, Inc
Category: homeopathic | Type: HUMAN OTC DRUG LABEL
Date: 20181221

ACTIVE INGREDIENTS: FERROSOFERRIC PHOSPHATE 12 [hp_X]/1 mL
INACTIVE INGREDIENTS: ALCOHOL; WATER

FERRUM PHOSPHORICUM 12X

ACTIVE INGREDIENTS (HPUS*): Ferrum Phosphoricum 12X.

INDICATIONS AND USAGE

USES: Temporarily relieves short, painful tickling cough &/or hard, dry cough.**

PURPOSE

USES: Temporarily relieves short, painful tickling cough &/or hard, dry cough.**

DOSAGE AND ADMINISTRATION

DIRECTIONS: Adults & children above 12 years: 10 drops orally 3 times daily, or as directed by a health care professional.

KEEP OUT OF REACH OF CHILDREN

KEEP OUT OF THE REACH OF CHILDREN. In case of overdose (or accidental ingestion) get medical help or contact a Poison Control Center right away.

WARNINGS:

- Consult a physician for use in children under 12 years of age.
- IF PREGNANT OR BREAST-FEEDING, ask a health care professional before use.
- KEEP OUT OF THE REACH OF CHILDREN. In case of overdose (or accidental ingestion) get medical help or contact a Poison Control Center right away.
- A persistent cough may be a sign of a serious condition. If cough persists for more than 1 week, tends to recur, or is accompanied by fever, rash, or persistent headache, consult a doctor.
- Do not use if TAMPER EVIDENT seal is broken or missing.

INACTIVE INGREDIENTS: Ethyl Alcohol USP, Purified Water.

QUESTIONS & COMMENTS?

Natural Creations, Inc. / Woodbine, IA 51579 / 712-647-1600

REFERENCES

*The letters "HPUS" indicate the component in this product is officially monographed in the Homeopathic Pharmacopeia of the United States.

**Claims based on traditional homeopathic practice, not accepted medical evidence. Not FDA evaluated.

PACKAGE LABEL

NDC:43406-0402-1

FERRUM PHOSPHORICUM 12X

HOMEOPATHIC

1 fl oz (30mL) / 20% Alcohol